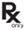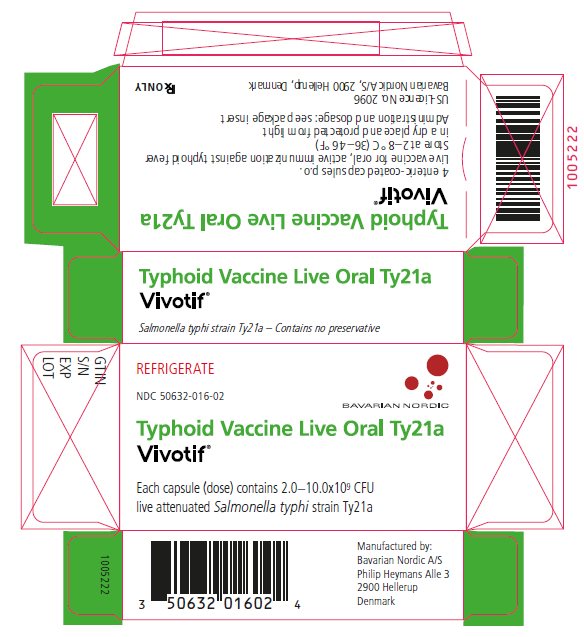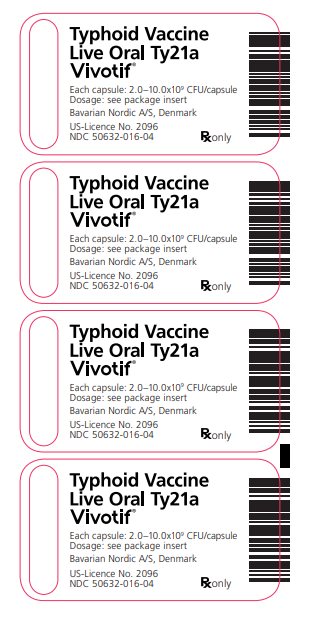 DRUG LABEL: Vivotif
NDC: 50632-016 | Form: CAPSULE, COATED
Manufacturer: Bavarian Nordic A/S
Category: other | Type: VACCINE LABEL
Date: 20250207

ACTIVE INGREDIENTS: SALMONELLA TYPHI TY21A LIVE ANTIGEN 6000000000 [CFU]/1 1
INACTIVE INGREDIENTS: ASCORBIC ACID; LACTOSE, UNSPECIFIED FORM; SUCROSE; AMINO ACIDS, SOURCE UNSPECIFIED; MAGNESIUM STEARATE

Typhoid Vaccine Live Oral Ty21a
Vivotif®

Description

Vivotif (Typhoid Vaccine Live Oral Ty21a) is a live attenuated vaccine for oral administration only. The vaccine contains the attenuated strain Salmonella typhi Ty21a (1,2).

Vivotif is manufactured by Bavarian Nordic A/S Denmark. The vaccine strain is grown in fermenters under controlled conditions in medium containing a digest of yeast extract, an acid digest of casein, dextrose and galactose. The bacteria are collected by centrifugation, mixed with a stabilizer containing sucrose, ascorbic acid and amino acids, and lyophilized. The lyophilized bacteria are mixed with lactose and magnesium stearate and filled into gelatin capsules which are coated with an organic solution to render them resistant to dissolution in stomach acid. The enteric-coated, salmon/white capsules are then packaged in 4-capsule blisters for distribution. The contents of each enteric-coated capsule are shown in Table 1.

Table 1: Contents of one enteric-coated capsule of Vivotif (Typhoid Vaccine Live Oral Ty21a)
Viable S. typhi Ty21a | 2.0–10.0x10^9 colony-forming units*
Non-viable S. typhi Ty21a | 5‑50x10^9 bacterial cells
Sucrose | 3.3 – 34.2 mg
Ascorbic acid | 0.2 – 2.4 mg
Amino acid mixture | 0.3 – 3.0 mg
Lactose | up to 180 - 200 mg
Magnesium stearate | 3.6–4.0 mg
*Vaccine potency (viable cell counts per capsule) is determined by inoculation of agar plates with appropriate dilutions of the vaccine suspended in physiological saline.

Clinical Pharmacology

Salmonella typhi is the etiological agent of typhoid fever, an acute, febrile enteric disease. Typhoid fever continues to be an important disease in many parts of the world. Travelers entering infected areas are at risk of contracting typhoid fever following the ingestion of contaminated food or water. Typhoid fever is considered to be endemic in most areas of Central and South America, the African continent, the Near East and the Middle East, Southeast Asia and the Indian subcontinent (3). There are approximately 500 cases of typhoid fever per year diagnosed in the United States (4). In 62% of these patients (data from 1975–1984) the disease was acquired outside of the United States while in 38% of the patients the disease was acquired within the United States (5). Of 340 cases acquired in the United States between 1977 and 1979, 23% of the cases were associated with typhoid carriers, 24% were due to food outbreaks, 23% were associated with the ingestion of contaminated food or water, 6% due to household contact with an infected person and 4% following exposure to S. typhi in a laboratory setting (6).

The majority of typhoid cases respond favorably to antibiotic therapy. However, the emergence of multi-drug resistant strains has greatly complicated therapy and cases of typhoid fever that are treated with ineffective drugs can be fatal (7). Approximately 2–4% of acute typhoid cases result in the development of a chronic carrier state (8). These non-symptomatic carriers are the natural reservoir for S. typhi and can serve to maintain the disease in its endemic state or to directly infect individuals (3).

Virulent strains of S. typhi upon ingestion are able to pass through the stomach acid barrier, colonize the intestinal tract, penetrate the lumen and enter the lymphatic system and blood stream, thereby causing disease. One possible mechanism by which disease may be prevented is by evoking a local immune response in the intestinal tract. Such local immunity may be induced by oral ingestion of a live attenuated strain of S. typhi undergoing an aborted infection. The ability of S. typhi to cause disease and to induce a protective immune response is dependent upon the bacteria possessing a complete lipopolysaccharide (1). The S. typhi Ty21a vaccine strain, by virtue of a reduction in enzymes essential for lipopolysaccharide biosynthesis, is restricted in its ability to produce complete lipopolysaccharide (1,2). However, a sufficient quantity of complete lipopolysaccharide is synthesized to evoke a protective immune response. Despite low levels of lipopolysaccharide synthesis, the cells lyse before regaining a virulent phenotype due to the intracellular build-up of intermediates during lipopolysaccharide synthesis (1,2).

Results from clinical studies indicate that adults and children greater than 6 years of age may be protected against typhoid fever following the oral ingestion of 4 doses of Vivotif (Typhoid Vaccine Live Oral Ty21a). The efficacy of the S. typhi Ty21a strain has been evaluated in a series of randomized, double-blind, controlled field trials. Suspected typhoid cases, detected by passive surveillance, were confirmed bacteriologically either by blood or bone marrow culture. The first trial was performed in Alexandria, Egypt with a study population of 32,388 children aged 6 to 7 years. 3 doses of vaccine, in the form of a freshly reconstituted suspension administered after ingestion of 1 g of bicarbonate, were given on alternate days. Immunization resulted in a 95% decrease [95% confidence interval (CI) = 77%–99%] in the incidence of typhoid fever over a 3-year period of surveillance (9). A series of field trials were subsequently performed in Santiago, Chile to evaluate efficacy when the vaccine strain was administered in the form of an acid-resistant enteric-coated capsule. The initial trial involved 82,543 school-aged children, and compared 1 or 2 doses of vaccine given one week apart. After 24 months of surveillance vaccine efficacy was 29% (95% CI = 4%–47%) for the single dose schedule and 59% (95% CI = 41%– 71%) for the 2-dose schedule (10). A further field trial was performed in Santiago, Chile involving 109,594 school-aged children (11). 3 doses of enteric-coated capsules were administered either on alternate days (short immunization schedule) or 21 days apart (long immunization schedule). Following 36 months of surveillance vaccination resulted in a 67% (95% CI = 47%–79%) decrease in the incidence of typhoid fever in the short immunization schedule group and a 49% reduction (95% CI = 24%–66%) in the long immunization schedule group. After 48 months of surveillance the short immunization schedule resulted in a 69% (95% CI = 55%–80%) decrease in typhoid fever (12). An undiminished level of protection was observed during the fifth year of surveillance. A field trial was next conducted in Santiago, Chile to determine the relative efficacy of 2, 3 and 4 doses of enteric-coated vaccine administered on alternate days to school-aged children. Relative vaccine efficacy as determined by comparison of disease incidence within the 3 vaccinated groups was highest for the 4 dose regimen (13). The incidence of typhoid fever per 105 study subjects was 160.5 (95% CI = 130–191) for the 3 dose regimen versus 95.8 (95% CI = 71–121) for the 4 dose regimen (p<0.004). An additional field trial to determine vaccine efficacy was conducted in Plaju, Indonesia involving 20,543 individuals approximately 3 to 44 years of age (14). Due to logistical considerations 3 doses of enteric-coated capsules were administered at weekly intervals, a schedule known to provide suboptimal protection (11). After 30 months of surveillance vaccine efficacy for all age groups was 42% (95% CI = 23%–57%). Vaccine organisms can be shed transiently in the stool of vaccine recipients (16). However, secondary transmission of vaccine organisms has not been documented. Ty21a has not been isolated from blood cultures following immunization. At present, the precise mechanism(s) by which Vivotif confers protection against typhoid fever is unknown. However, it is known that immunization of adult subjects can elicit a humoral anti-S. typhi LPS antibody response. Taking advantage of this fact, the seroconversion rate (defined as a ≥0.15 increase in optical density units over baseline determined in an ELISA) was compared in an open study between adults living in an endemic area (Chile) and non-endemic areas (United States and Switzerland) after the ingestion of 3 doses of vaccine. Comparable seroconversion rates were seen between these groups (15). S. typhi Ty21a cultured in medium not containing BHI induced an anti-S. typhi LPS antibody response comparable to that obtained with vaccine organisms cultured in medium containing BHI (15). Challenge studies in North American volunteers have shown that the Ty21a strain is capable of providing significant protection to an experimental challenge of S. typhi (16). Because of the very low incidence of typhoid fever in United States citizens, efficacy studies are not currently feasible in this population. However, the above observations support the expectation that Vivotif will provide protection to recipients from non-typhoid endemic areas such as the United States.

Indications and Usage

Vivotif (Typhoid Vaccine Live Oral Ty21a) is indicated for immunization of adults and children greater than 6 years of age against disease caused by Salmonella typhi. Routine typhoid vaccination is not recommended in the United States of America. Selective immunization against typhoid fever is recommended for the following groups: 1) travelers to areas in which there is a recognized risk of exposure to S. typhi, 2) persons with intimate exposure (e.g. household contact) to a S. typhi carrier, and 3) microbiology laboratorians who work frequently with S. typhi (7). There is no evidence to support the use of typhoid vaccine to control common source outbreaks, disease following natural disasters or in persons attending rural summer camps.

Not all recipients of Vivotif will be fully protected against typhoid fever. Vaccinated individuals should continue to take personal precautions against exposure to typhoid organisms. The vaccine will not afford protection against species of Salmonella other than Salmonella typhi or other bacteria that cause enteric disease. The vaccine is not suitable for treatment of acute infections with S. typhi.

Contraindications

Hypersensitivity to any component of the vaccine or the enteric-coated capsule. The vaccine should not be administered to persons during an acute febrile illness. Safety of the vaccine has not been demonstrated in persons deficient in their ability to mount a humoral or cell-mediated immune response, due to either a congenital or acquired immunodeficient state including treatment with immunosuppressive or antimitotic drugs. The vaccine should not be administered to these persons regardless of benefits.

Warnings

Vivotif (Typhoid Vaccine Live Oral Ty21a) is not to be taken during an acute gastrointestinal illness. The vaccine should not be administered to individuals receiving sulfonamides and antibiotics since these agents may be active against the vaccine strain and prevent a sufficient degree of multiplication to occur in order to induce a protective immune response. Postpone taking the vaccine if persistent diarrhea or vomiting is occurring. Unless a complete immunization schedule is followed, an optimum immune response may not be achieved. Not all recipients of Vivotif will be fully protected against typhoid fever. Vaccinated individuals should continue to take personal precautions against exposure to typhoid organisms, i.e. travelers should take all necessary precautions to avoid contact or ingestion of potentially contaminated food or water.

Drug Interactions

Several anti-malaria drugs, such as mefloquine, chloroquine and proguanil (not approved for use in US) possess anti-bacterial activity which may interfere with the immunogenicity of Vivotif (17,18). To determine the effect of these anti-malaria drugs on the humoral IgG or IgA anti-S. typhi immune response, healthy adult subjects were given mefloquine (250 mg at weekly intervals; N = 30) chloroquine (500 mg at weekly intervals; N = 30) or proguanil (200 mg daily; N = 30) together with the S. typhi Ty21a vaccine strain (19). Concomitant treatment with mefloquine or chloroquine did not result in a significant reduction in the serum anti-S. typhi immune response compared to subjects receiving vaccine strain only (N = 45). The simultaneous administration of proguanil did effect a significant decrease in the immune response rate. These findings indicate that mefloquine and chloroquine can be administered together with Vivotif. Proguanil should be administered only if 10 days or more have elapsed since the final dose of Vivotif was ingested. The concomitant administration of oral polio vaccine or yellow fever vaccine does not suppress the immune response elicited by the Ty21a vaccine strain (19). There are no data regarding simultaneous administration of other parenteral vaccines or immunoglobulins with Vivotif.

Precautions

General

The health care provider should take all necessary precautions to ensure the safe and effective use of the vaccine. Patients should be questioned about previous reactions to this or similar products. The previous immunization history of the patient and current antibiotic usage should be obtained by the health care provider.

Information for Patients

It is essential that all 4 doses of vaccine be taken at the prescribed alternate day interval to obtain a maximal protective immune response. Vaccine potency is dependent upon storage under refrigeration [between 2 °C and 8 °C (35.6 °F – 46.4 °F)]. The vaccine should be stored under refrigeration at all times. It is essential to replace unused vaccine in the refrigerator between doses. The vaccine capsule should be swallowed approximately 1 hour before a meal with a cold or luke-warm [temperature not to exceed body temperature, e.g., 37 °C (98.6 °F)] drink. Care should be taken not to chew the vaccine capsule. The vaccine capsule should be swallowed as soon after placing in the mouth as possible.

Not all recipients of Vivotif (Typhoid Vaccine Live Oral Ty21a) will be fully protected against typhoid fever. Travelers should take all necessary precautions to avoid contact or ingestion of potentially contaminated food or water. Several anti-malaria drugs, such as mefloquine, chloroquine and proguanil (not approved for use in US) possess antibacterial activity which may interfere with the immunogenicity of Vivotif. Clinical results (see Warnings – Drug- Interactions) indicate that mefloquine and chloroquine can be administered together with Vivotif. Proguanil should be administered only if 10 days or more have elapsed since the final dose of Vivotif was ingested. Any serious adverse reactions related to the administration of the vaccine should be reported to your health care provider. You may also report an adverse reaction directly to the Vaccine Adverse Event Reporting System (1–800–822–7967) (20). Your health care provider should inform you of the benefits and risks of the vaccine, the importance of taking all 4 capsules in the correct schedule, and the importance of proper storage temperature of the capsules.

Carcinogenesis, Mutagenesis, Impairment of Fertility

Long-term studies in animals with Vivotif have not been performed to evaluate carcinogenic potential, mutagenic potential or impairment of fertility.

Pregnancy

Category C
Animal reproduction studies have not been conducted with Vivotif. It is not known whether Vivotif can cause fetal harm when administered to pregnant women or can affect reproduction capacity. Vivotif should be given to a pregnant woman only if clearly needed.

Nursing Mothers

There is no data to warrant the use of this product in nursing mothers. It is not known if Vivotif is excreted in human milk.

Pediatric Use

The safety and efficacy of Vivotif has not been established in children under 6 years of age. This product is not indicated for use in children under 6 years of age.

Adverse Reactions

More than 1.4 million doses of Ty21a have been administered in controlled clinical trials and more than 150 million doses of Vivotif (Typhoid Vaccine Live Oral Ty21a) have been marketed world-wide. Active surveillance for adverse reactions of enteric-coated capsules was performed in a pilot study (21) and in a subgroup of a large field trial (14) involving a total of 483 individuals receiving 3 vaccine doses. The overall symptom rates from both studies when vaccinated with capsules were combined and shown to be: abdominal pain (6.4%), nausea (5.8%), headache (4.8%), fever (3.3%), diarrhea (2.9%), vomiting (1.5%) and skin rash (1.0%). Only the incidence of nausea occurred at a statistically higher frequency in the vaccinated group as compared to the placebo group (14). Administration of vaccine doses more than 5- fold higher than the currently recommended dose caused only mild reactions in an open study involving 155 healthy adult males (16).

Post-marketing surveillance has revealed that adverse reactions are infrequent and mild (17). Adverse reactions reported to the manufacturer during 1991–1995, during which time over 60 million doses (capsules) were administered, included: diarrhea (N = 45), abdominal pain (N = 42), nausea (N = 35), fever (N = 34), headache (N = 26), skin rash (N = 26), vomiting (N = 18), or urticaria in the trunk and/or extremities (N = 13). One isolated, non-fatal anaphylactic shock considered to be an allergic reaction to the vaccine was reported.

To report SUSPECTED ADVERSE REACTIONS, contact Bavarian Nordic A/S at 1-833-365-9596 or contact the Vaccine Adverse Event Reporting System (VAERS) at 1-800-822-7967 or www.vaers.hhs.gov.

Dosage and Administration

One capsule is to be swallowed approximately 1 hour before a meal with a cold or luke-warm [temperature not to exceed body temperature, e.g., 37 °C (98.6 °F)] drink on alternate days, e.g., days 1, 3, 5 and 7. Immunization (ingestion of all 4 doses of Vivotif (Typhoid Vaccine Live Oral Ty21a) should be completed at least 1 week prior to potential exposure to S. typhi.

The blister containing the vaccine capsules should be inspected to ensure that the foil seal and capsules are intact. The vaccine capsule should not be chewed and should be swallowed as soon after placing in the mouth as possible. A complete immunization schedule is the ingestion of 4 vaccine capsules as described above.

Re-immunization

The optimum booster schedule for Vivotif has not been determined. Efficacy has been shown to persist for at least 5 years. Further, there is no experience with Vivotif as a booster in persons previously immunized with parenteral typhoid vaccine. It is recommended that a re-immunization dose consisting of 4 vaccine capsules taken on alternate days be given every 5 years under conditions of repeated or continued exposure to typhoid fever (7).

How Supplied

A single foil blister contains 4 doses of vaccine in a single package.

NDC 50632-016-04 and NDC 50632-016-02

Storage

Vivotif (Typhoid Vaccine Live Oral Ty21a) is not stable when exposed to ambient temperatures. Vivotif should therefore be shipped and stored between 2 °C and 8 °C (35.6 °F–46.4 °F). Each package of vaccine shows an expiration date. This expiration date is valid only if the product has been maintained at 2 °C–8 °C (35.6 °F–46.4 °F).

References

1. Germanier R., E. Fürer. Isolation and characterisation of Gal E mutant Ty21a of Salmonella typhi: a candidate strain for a live, oral typhoid vaccine. J. Infect. Dis. 131: 553–558, 1975.
2. Germanier R., E. Fürer. Characteristics of the attenuated oral vaccine strain S. typhi Ty21a. Develop. Biol. Standard 53: 3–7, 1983.
3. Miller S.I., E.L. Hohmann, D.A. Pegues. Salmonella (including Salmonella typhi). In: Principles and practice of infectious diseases. G.L. Mandell, J.E. Bennett, R. Dolin (ed.) fourth edition, Churchill Livingstone Inc. 2013–2033, 1995.
4. Centers for Disease Control. Summary of notifiable diseases, United States 1995. MMWR 44 (Supplement), 1996.
5. Ryan C.A., N.T. Hargrett-Bean, P.A. Blake. Salmonella typhi infections in the United States, 1975– 1984: Increasing role of foreign travel. Rev. Infect. Dis. 11: 1–8, 1989.
6. Taylor D.N., R.A. Pollard, P.A. Blake. Typhoid in the United States and the Risk to the International Traveler. J. Infect. Dis. 148: 599–602, 1983.
7. Recommendations of the Advisory Committee on Immunization Practices (ACIP): Typhoid Immunization. MMWR 43 (RR-14), 1994.
8. Ames W.R., M. Robbins. Age and sex as factors in the development of the typhoid carrier state, and a model for estimating carrier prevalence. Am. J. Public Health 33: 221–230, 1943.
9. Wahdan M.H., C. Sérié, Y. Cerisier, S. Sallam, R. Germanier. A controlled field trial of live Salmonella typhi strain Ty21a oral vaccine against typhoid: three-year results. J. Infect. Dis. 145: 292–296, 1982.
10. Black R.E., M.M. Levine, C. Ferreccio, M.L. Clements, C. Lanata, J. Rooney, R. Germanier, Chilean Typhoid Committee. Efficacy of one or two doses of Ty21a Salmonella typhi vaccine in enteric-coated capsules in a controlled field trial. Vaccine 8: 81–84, 1990.
11. Levine M.M., C. Ferreccio, R.E. Black, R. Germanier, Chilean Typhoid Committee. Large-Scale Field Trial of Ty21a Typhoid Vaccine Live Oral Ty21a in Enteric-Coated Capsule Formulation. Lancet 1: 1049– 1052, 1987.
12. Levine M.M., C. Ferreccio, R.E. Black, C.O. Tacket, R. Germanier, Chilean Typhoid Committee. Progress in vaccines against typhoid fever. Rev. Infect. Dis. 11 (Supplement 3): S552–S567, 1989.
13. Ferreccio C., M.M. Levine, H. Rodriguez, R. Contreras, Chilean Typhoid Committee. Comparative efficacy of two, three, or four doses of Ty21a live oral typhoid vaccine in enteric-coated capsules: a field trial in endemic area. J. Infect. Dis. 159: 766–769, 1989.
14. Simanjuntak C.H., F.P. Paleologo, N.H. Punjabi, R. Darmowigoto, Soeprawoto, H. Totosudirjo, P. Haryanto, E. Suprijanto, N.D. Witham, S.L. Hoffman. Oral immunisation against typhoid fever in Indonesia with Ty21a vaccine. Lancet 338: 1055–1059, 1991.
15. Data on File, Swiss Serum and Vaccine Institute Berne, Switzerland.
16. Gilman R.H., R.B. Hornick, W.E. Woodward, H.L. DuPont, M.J. Snyder, M.M. Levine, J.P. Libonati. Evaluation of a UDP-glucose-4-epimeraseless mutant of Salmonella typhi as a live oral vaccine. J. Infect. Dis. 136: 717–723, 1977.
17. Cryz S.J. Jr., Post-marketing experience with live oral Ty21a Vaccine. Lancet; 341: 49–50, 1993. Data on File, Swiss Serum and Vaccine Institute Berne, Switzerland.
18. Horowitz H., CA. Carbonaro, Inhibition of the Salmonella typhi oral vaccine strain Ty21a, by mefloquine and chloroquine. J. Infect. Dis. 166: 1462–1464, 1992.
19. Kollaritsch H., J.U. Que, C. Kunz, G. Wiedermann, C. Herzog, S.J. Cryz Jr. Safety and immunogenicity of live oral cholera and typhoid vaccines administered alone or in combination with anti- malarial drugs, oral polio vaccine or yellow fever vaccine. J. Infect. Dis. 175: 871–875, 1997.
20. Vaccine Adverse Event Reporting System – United States. MMWR 39: 730–733, 1990.
21. Levine M.M., R.E. Black, C. Ferreccio, M.L. Clements, C. Lanata, J. Rooney, R. Gemanier. The efficacy of attenuated Salmonella typhi oral vaccine strain Ty21a evaluated in controlled field trials. In: Development of Vaccines and Drugs against Diarrhea. 11th Noble Conference, Stockholm, 1985, p. 90–101. J. Holmgren, A. Lindberg and R. Möllby (eds.). Studentlitteratur, Lund, Sweden, 1986.

Vivotif® is a registered trademark of Bavarian Nordic A/S
US-License No. 2096

Manufactured by:
Bavarian Nordic A/S, Philip Heymans Alle 3
2900 Hellerup, Denmark

©2023 Bavarian Nordic A/S. All rights reserved.

Version: February 2025

PRINCIPAL DISPLAY PANEL - Carton Label

Carton Label

REFRIGERATE

NDC 50632-016-02

BAVARIAN NORDIC

Typhoid Vaccine Live Oral Ty21a
Vivotif®

Each capsule (dose) contains 2.0-10.0x10^9 CFU
live attenuated Salmonella typhi strain Ty21a

Manufactured by:
Bavarian Nordic A/S
Philip Heymans Alle 3
2900 Hellerup
Denmark

GTIN
S/N
EXP
LOT

Typhoid Vaccine Live Oral Ty21a
Vivotif®

Salmonella typhi strain Ty21a - Contains no preservative

Typhoid Vaccine Live Oral Ty21a
Vivotif®

4 enteric-coated capsules p.o.
Live vaccine for oral, active immunization against typhoid fever
Store at 2-8 °C (36-46 °F)
in a dry place and protected from light
Administration and dosage: see package insert

US-Licence No. 2096
Bavarian Nordic A/S, 2900 Hellerup, Denmark

Rx ONLY

PRINCIPAL DISPLAY PANEL - Blister Label

Blister Label

Typhoid Vaccine
Live Oral Ty21a
Vivotif®

Each capsule: 2.0-10.0x10^9 CFU/capsule
Dosage: see package insert

Bavarian Nordic A/S, Denmark

US-Licence No. 2096
NDC 50632-016-04

Rx only